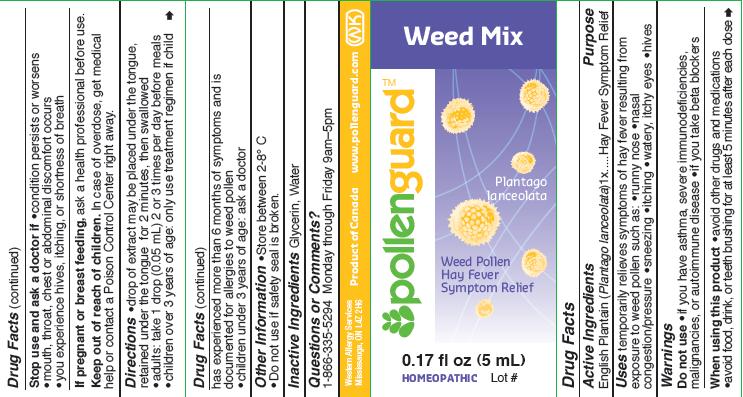 DRUG LABEL: Pollen Guard Weed Mix
NDC: 76097-004 | Form: LIQUID
Manufacturer: Western Allergy Services Ltd.
Category: homeopathic | Type: HUMAN OTC DRUG LABEL
Date: 20110927

ACTIVE INGREDIENTS: PLANTAGO LANCEOLATA POLLEN 1 [hp_X]/5 mL
INACTIVE INGREDIENTS: GLYCERIN; WATER

ACTIVE INGREDIENT

English Plantain (Plantago lanceolata) 1X

PURPOSE

Hay Fever Symptom Relief

INDICATIONS AND USAGE

temporarily relieves symptoms of hay fever resulting from exposure to weed pollen such as:

- runny nose
- nasal congestion/pressure
- sneezing
- itching
- water, itchy eyes
- hives

Do not use

- if you have asthma, severe immunodeficiencies, malignancies, or autoimmune disease
- if you take beta blockers

When using this product

- avoid other drugs and medications
- avoid food, drink, or teeth brushing for at least 5 minutes after each dose

Stop use and ask a doctor if

- condition persists or worsens
- mouth, throat, chest or abdominal discomfort occurs
- you experience hives, itching, or shortness of breath

PREGNANCY OR BREAST FEEDING

If pregnant or breast feeding, ask a health professional before use.

Keep out of reach of children. In case of overdose, get medical help or contact a Poison Control Center right away.

Directions

- drop of extract may be placed under tongue, retained under the tongue for 2 minutes, then swallowed
- adults: take 1 drop (0.05 mL) 2 or 3 times per day before meals
- children over 3 years of age: only use treatment regimen if child has experienced more than 6 months of symptoms and is documented for allergies to weed pollen
- children under 3 years of age: ask a doctor

STORAGE AND HANDLING

- Store between 2-8 degrees C
- Do not use if safety seal is broken

INACTIVE INGREDIENT

Glycerin, Water

Questions or Comments?

1-866-335-5294 Monday through Friday 9am-5pm